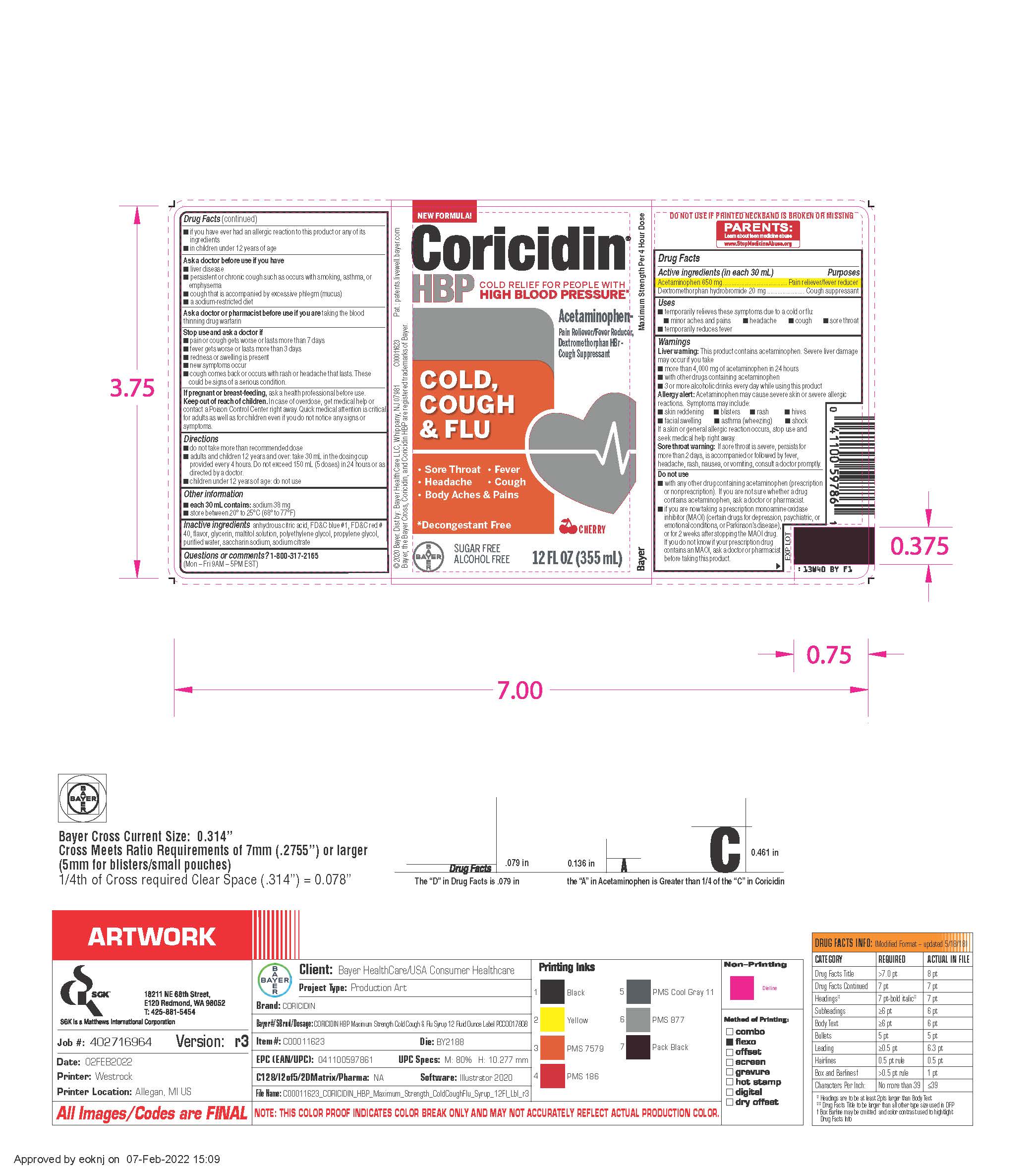 DRUG LABEL: Coricidin HBP Maximum Strength Cold, Cough and Flu
NDC: 11523-0093 | Form: LIQUID
Manufacturer: Bayer HealthCare LLC.
Category: otc | Type: HUMAN OTC DRUG LABEL
Date: 20241206

ACTIVE INGREDIENTS: ACETAMINOPHEN 650 mg/30 mL; DEXTROMETHORPHAN HYDROBROMIDE 20 mg/30 mL
INACTIVE INGREDIENTS: PROPYLENE GLYCOL; FD&C RED NO. 40; WATER; SACCHARIN SODIUM; SODIUM CITRATE; POLYETHYLENE GLYCOL, UNSPECIFIED; ANHYDROUS CITRIC ACID; FD&C BLUE NO. 1; GLYCERIN; MALTITOL

Coricidin HBP Maximum Strength Cold , Cough & Flu Liquid

Drug Facts

Active ingredients (in each 30 mL) | Purposes
Acetaminophen 650 mg | Pain reliever/fever reducer
Dextromethorphan hydrobromide 20 mg | Cough suppressant

Uses

- temporarily relieves these symptoms due to a cold or flu:
  - minor aches and pains
  - headache
  - cough
  - sore throat
- temporarily reduces fever

Warnings
Liver warning: This product contains acetaminophen. Severe liver damage may occur if you take
• more than 4,000 mg of acetaminophen in 24 hours
• with other drugs containing acetaminophen
• 3 or more alcoholic drinks every day while using this product

Allergy alert: Acetaminophen may cause severe skin or severe allergic reactions. Symptoms may include:

- skin reddening
- blisters
- rash
- hives
- facial swelling
- asthma (wheezing)
- shock

If a skin or general allergic reaction occurs, stop use and seek medical help right away.

Sore throat warning: If sore throat is severe, persists for more than 2 days, is accompanied or followed by fever, headache, rash, nausea, or vomiting, consult a doctor promptly.

Do not use

- with any other drug containing acetaminophen (prescription or nonprescription). If you are not sure whether a drug contains acetaminophen,ask a doctor or pharmacist.
- if you are now taking a prescription monoamine oxidase inhibitor (MAOI) (certain drugs for depression, psychiatric, or emotional conditions, or Parkinson's disease), or for 2 weeks after stopping the MAOI drug. If you do not know if your prescription drug contains an MAOI, ask a doctor or pharmacist before taking this product.
- if you have ever had an allergic reaction to this product or any of its ingredients
- in children under 12 years of age

Ask a doctor before use if you have

- liver disease
- persistent or chronic cough such as occurs with smoking, asthma or emphysema
- cough that is accompanied with excessive phlegm (mucus)
- a sodium-restricted diet

Ask a doctor or pharmacist before use if you are taking the blood thinning drug warfarin

Stop use and ask a doctor if

- pain or cough gets worse or lasts more than 7 days
- fever gets worse or lasts more than 3 days
- redness or swelling is present
- new symptoms occur
- cough comes back or occurs with rash or headache that lasts. These could be signs of a serious condition.

PREGNANCY OR BREAST FEEDING

If pregnant or breast-feeding, ask a health professional before use.

Keep out of reach of children. In case of overdose, get medical help or contact a Poison Control Center right away. Quick medical attention is critical for adults as well as for children even if you do not notice any signs or symptoms.

Directions

- do not take more than recommended dose
- adults and children 12 years and over: take 30 mL in the dosing cup provided every 4 hours. Do not exceed 150 mL (5 doses) in 24 hours or as directed by a doctor.
- children under 12 years of age: do not use

Other information
• each 30 mL contains: sodium 38 mg
• store between 20º to 25ºC (68º to 77ºF)

INACTIVE INGREDIENT

Inactive ingredients anhydrous citric acid, FD&C blue #1, FD&C red # 40, flavor, glycerin, maltitol solution, polyethylene glycol, propylene glycol, purified water, saccharin sodium, sodium citrate

Questions or comments? 1-800-317-2165 (Mon – Fri 9AM – 5PM EST)

PACKAGE LABEL

New Formula!

Coricidin®

HBP

COLD RELIEF FOR PEOPLE WITH

HIGH BLOOD PRESSURE†

MAXIMUM STRENGTH

NIGHTTIME

COLD

& FLU

Relieves

Body Aches & Pains

Headache, Fever,

Cough, Sore Throat,

SUGAR FREE

Alcohol Free

Cherry

†Decongestant Free

Acetaminophen -

Pain Reliever/Fever Reducer

Dextromethorphan HBr-

Cough Suppressant

12 FL OZ (355 mL)